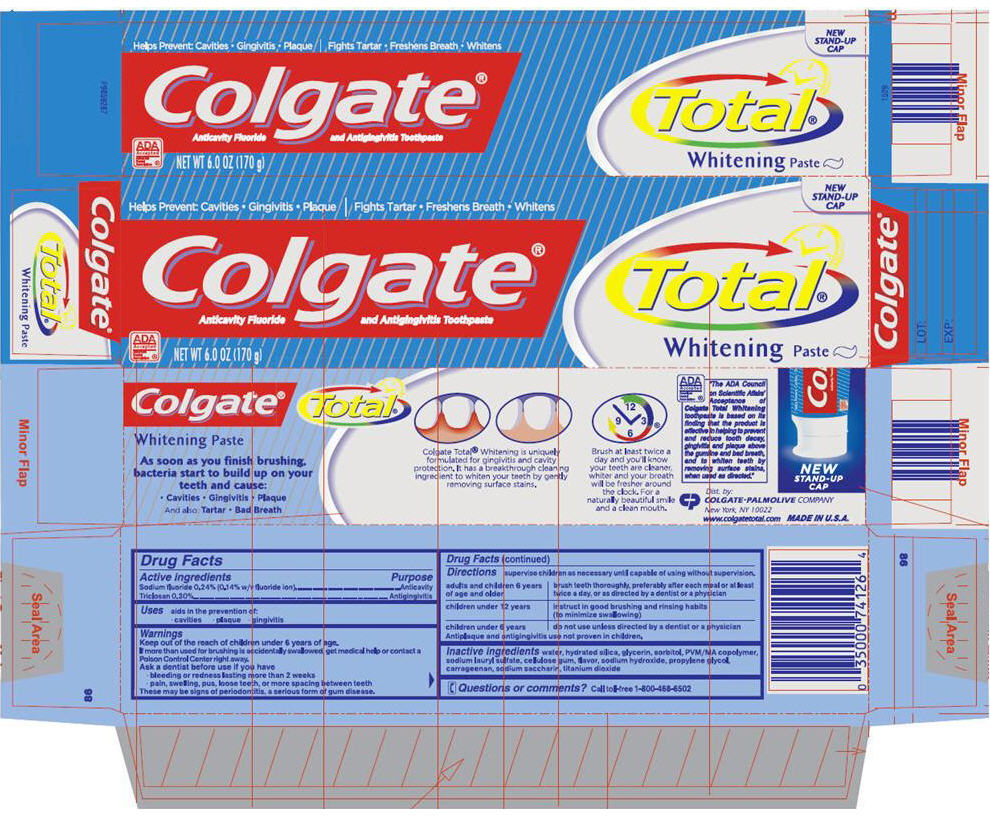 DRUG LABEL: Total Whitening
NDC: 67659-300 | Form: PASTE
Manufacturer: Team Technologies, Inc
Category: otc | Type: HUMAN OTC DRUG LABEL
Date: 20160518

ACTIVE INGREDIENTS: SODIUM FLUORIDE 1.4 mg/1 g; TRICLOSAN 3 mg/1 g
INACTIVE INGREDIENTS: WATER; HYDRATED SILICA; GLYCERIN; SORBITOL; SODIUM LAURYL SULFATE; CARBOXYMETHYLCELLULOSE SODIUM, UNSPECIFIED FORM; SODIUM HYDROXIDE; PROPYLENE GLYCOL; CARRAGEENAN; SACCHARIN SODIUM; TITANIUM DIOXIDE

Colgate®
Total®
Whitening Paste

Drug Facts

ACTIVE INGREDIENT

Active ingredients | Purpose
Sodium fluoride 0.24% (0.14% w/v fluoride ion) | Anticavity
Triclosan 0.30% | Antigingivitis

Uses

aids in the prevention of:

- cavities
- plaque
- gingivitis

Warnings

KEEP OUT OF REACH OF CHILDREN

Keep out of the reach of children under 6 years of age.

If more than used for brushing is accidentally swallowed, get medical help or contact a Poison Control Center right away.

Ask a dentist before use if you have

- bleeding or redness lasting more than 2 weeks
- pain, swelling, pus, loose teeth, or more spacing between teeth

These may be signs of periodontitis, a serious form of gum disease.

Directions

supervise children as necessary until capable of using without supervision.

adults and children 6 years of age and older | brush teeth thoroughly, preferably after each meal or at least twice a day, or as directed by a dentist or a physician
children under 12 years | instruct in good brushing and rinsing habits (to minimize swallowing)
children under 6 years | do not use unless directed by a dentist or a physician

Antiplaque and antigingivitis use not proven in children.

Inactive ingredients

water, hydrated silica, glycerin, sorbitol, PVM/MA copolymer, sodium lauryl sulfate, cellulose gum, flavor, sodium hydroxide, propylene glycol, carrageenan, sodium saccharin, titanium dioxide

Questions or comments?

Call toll-free 1-800-468-6502

Dist. by:
COLGATE-PALMOLIVE COMPANY
New York, NY 10022

www.colgatetotal.com

PRINCIPAL DISPLAY PANEL - 170 g Tube Carton

NEW
STAND-UP
CAP

Helps Prevent Cavities • Gingivitis • Plaque
Fights Tartar Buildup • Whitens

Colgate®
Anticavitiy Fluoride and Antigingivitis Toothpaste

Total®
Whitening Paste

ADA
Accepted
American
Dental
Association ®

NET WT 6.0 OZ (170 g)